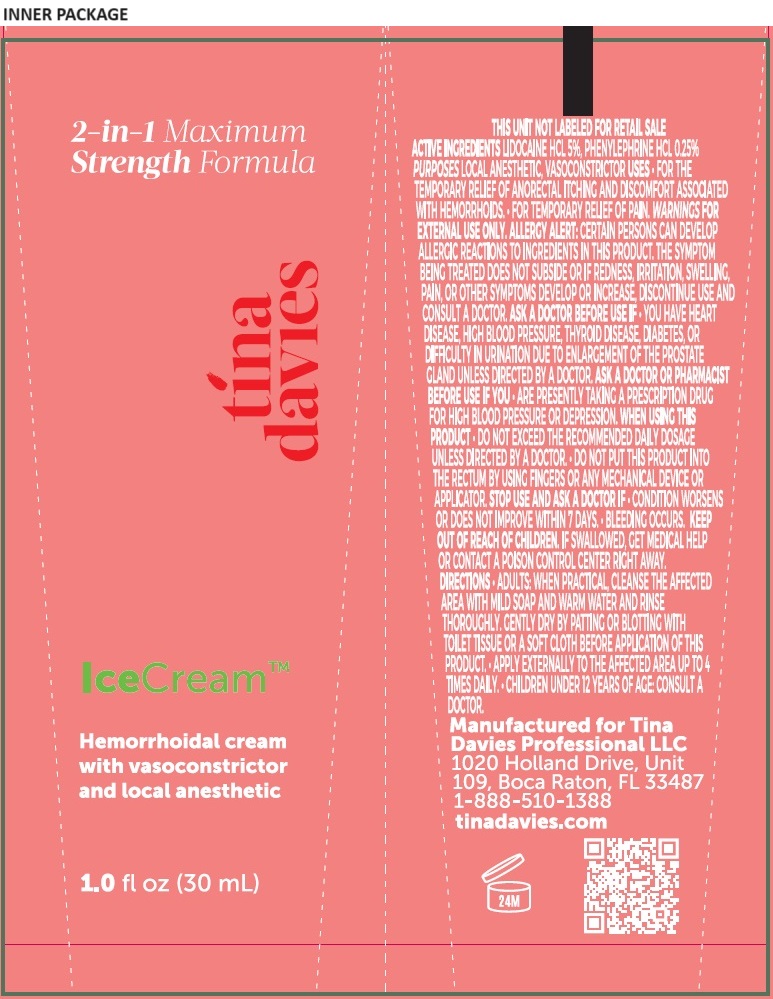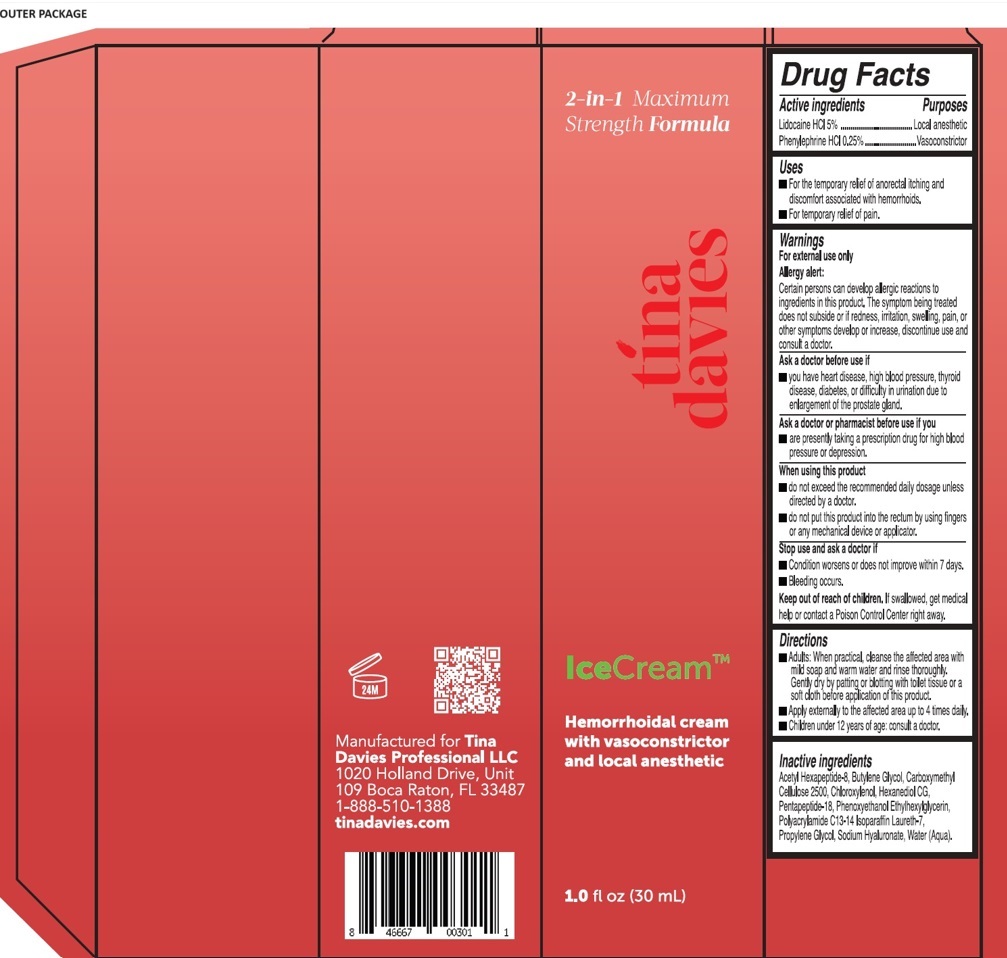 DRUG LABEL: Tina Davies IceCream
NDC: 84313-001 | Form: CREAM
Manufacturer: TINA DAVIES PROFESSIONAL LLC
Category: otc | Type: HUMAN OTC DRUG LABEL
Date: 20240530

ACTIVE INGREDIENTS: LIDOCAINE HYDROCHLORIDE 5 g/100 mL; PHENYLEPHRINE HYDROCHLORIDE 0.25 g/100 mL
INACTIVE INGREDIENTS: ACETYL HEXAPEPTIDE-8 AMIDE; BUTYLENE GLYCOL; CARBOXYMETHYLCELLULOSE CALCIUM; CHLOROXYLENOL; HEXANEDIOL; PENTAPEPTIDE-18; PHENOXYETHANOL; ETHYLHEXYLGLYCERIN; POLYACRYLAMIDE (10000 MW); C12-14 ISOPARAFFIN; LAURETH-7; PROPYLENE GLYCOL; HYALURONATE SODIUM; WATER

tina davies IceCream

Active ingredients

Lidocaine HCl 5%

Phenylephrine HCl 0.25%

Purpose

Local anesthetic

Vasoconstrictor

Uses

• For the temporary relief of anorectal itching and discomfort associated with hemorrhoids.
• For temporary relief of pain.

Warnings

For external use only
Allergy alert:
Certain persons can develop allergic reactions to ingredients in this product. The symptom being treated does not subside or if redness, irritation, swelling, pain, or other symptoms develop or increase, discontinue use and consult a doctor.
Ask a doctor before use if
• you have heart disease, high blood pressure, thyroid disease, diabetes, or difficulty in urination due to enlargement of the prostate gland.
Ask a doctor or pharmacist before use if you
• are presently taking a prescription drug for high blood pressure or depression.
When using this product
• do not exceed the recommended daily dosage unless directed by a doctor.
• do not put this product into the rectum by using fingers or any mechanical device or applicator.
Stop use and ask a doctor if
• Condition worsens or does not improve within 7 days.
• Bleeding occurs.

Keep out of reach of children. If swallowed, get medical help or contact a Poison Control Center right away.

Directions

• Adults: When practical, cleanse the affected area with mild soap and warm water and rinse thoroughly. Gently dry by patting or blotting with toilet tissue or a soft cloth before application of this product.
• Apply externally to the affected area up to 4 times daily.
• Children under 12 years of age: consult a doctor.

Inactive ingredients

Acetyl Hexapeptide-8, Butylene Glycol, Carboxymethyl Cellulose 2500, Chloroxylenol, Hexanediol CG, Pentapeptide-18, Phenoxyethanol, Ethylhexylglycerin, Polyacrylamide, C13-14 Isoparaffin, Laureth-7, Propylene Glycol, Sodium Hyaluronate, Water (Aqua).

2-in-1 Maximum

Strength Formula

Hemorrhoidal cream

with vasoconstrictor

and local anesthetic

Manufactured for Tina Davies Professional LLC

1020 Holland Drive, Unit

109 Boca Raton, FL 33487

1-888-510-1388

tinadavies.com